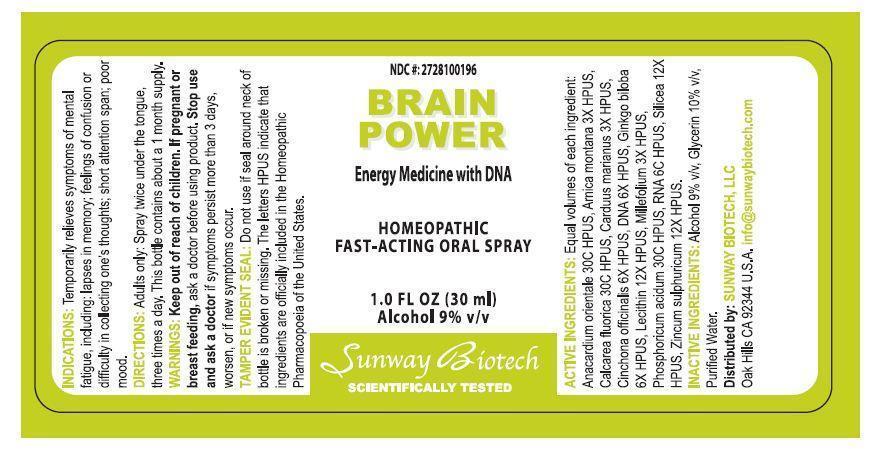 DRUG LABEL: Brain Power
NDC: 27281-001 | Form: SPRAY
Manufacturer: Sunway Biotech LLC
Category: homeopathic | Type: HUMAN OTC DRUG LABEL
Date: 20131120

ACTIVE INGREDIENTS: SEMECARPUS ANACARDIUM JUICE 30 [hp_C]/30 mL; ARNICA MONTANA 1.5 [hp_C]/30 mL; CALCIUM FLUORIDE 30 [hp_C]/30 mL; SILYBUM MARIANUM SEED OIL 1.5 [hp_C]/30 mL; CINCHONA OFFICINALIS BARK 3 [hp_C]/30 mL; HERRING SPERM DNA 3 [hp_C]/30 mL; GINKGO 3 [hp_C]/30 mL; EGG PHOSPHOLIPIDS 6 [hp_C]/30 mL; ACHILLEA MILLEFOLIUM 1.5 [hp_C]/30 mL; PHOSPHORIC ACID 30 [hp_C]/30 mL; SACCHAROMYCES CEREVISIAE RNA 6 [hp_C]/30 mL; SILICON DIOXIDE 6 [hp_C]/30 mL; ZINC SULFATE HEPTAHYDRATE 6 [hp_C]/30 mL
INACTIVE INGREDIENTS: ALCOHOL; GLYCERIN; WATER

ACTIVE INGREDIENT

Active Ingredients: Equal volumes of each ingredient: Anacardium Orientale 30C HPUS, Arnica Montana 3X HPUS, Calcarea Fluorica 30C HPUS, Carduus Marianus 3X HPUS, Cinchona Officinalis 6X HPUS, DNA 6X HPUS, Ginkgo Biloba 6X HPUS, Lecithin 12X HPUS, Millefolium 3X HPUS, Phosphoricum Acidum 30C HPUS, RNA 6C HPUS, Silicea 12X HPUS, Zincum Sulphuricum 12X HPUS.

PURPOSE

NDC #: 2728100196

BRAIN POWER

Energy Medicine with DNA

Homeopathic Fast-Acting Oral Spray

1.0 Fl. Oz. (30 mL)

Alcohol 9% v/v

Keep out of reach of children.

INDICATIONS AND USAGE

Indications: Temporarily relieves symptoms of mental fatigue, including: lapses in memory; feelings of confusion or difficulty collecting one's thoughts; short attention span; poor mood.

DOSAGE AND ADMINISTRATION

Directions: Adults only: spray twice under the tongue, three times a day. This bottle contains about a 1 month supply.

WARNINGS

Warnings: Keep out of reach of children. If pregnant or breast feeding, ask a doctor before using product. Stop use and ask a doctor if symptoms persist more than 3 days, worsen, or if new symptoms occur.

OTHER SAFETY INFORMATION

Tamper Evident Seal: Do not use if seal around neck of bottle is broken or missing. The letters HPUS indicate that ingredients are officially included in the Homeopathic Pharmacopoeia of the United States.

Distributed By:

SUNWAY BIOTECH LLC

Oak HIlls, CA 92344 U.S.A.

info@sunwaybiotech.com

INACTIVE INGREDIENT

Inactive Ingredients: Alcohol 9% v/v, Glycerin 10% v/v, Purified Water.